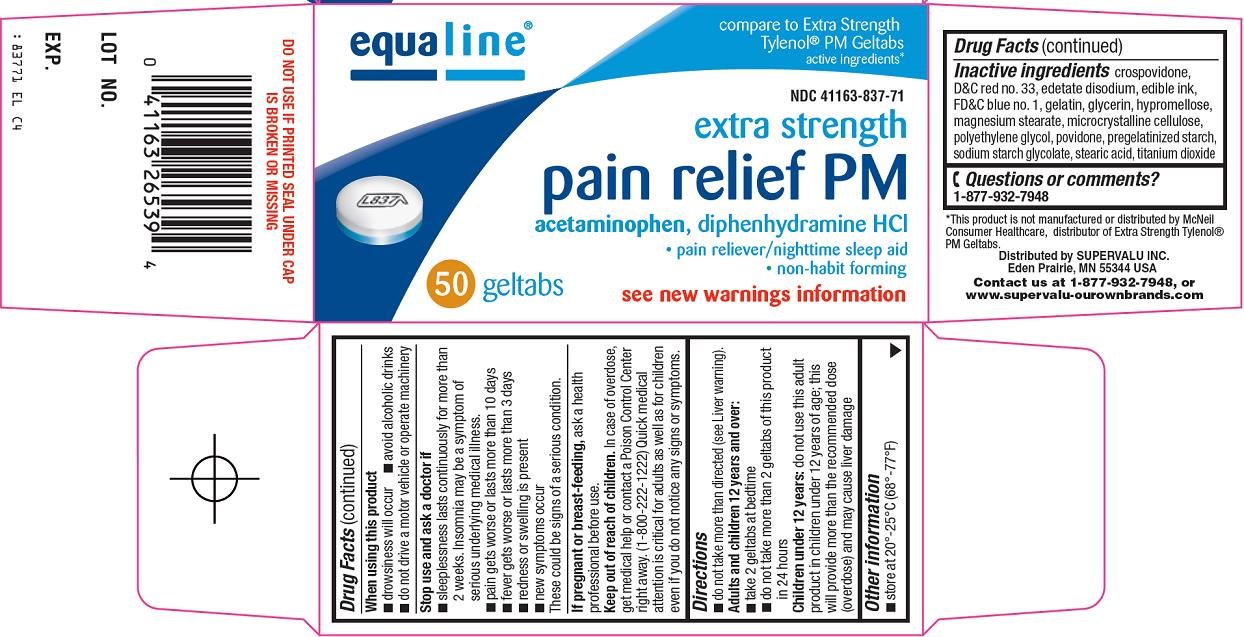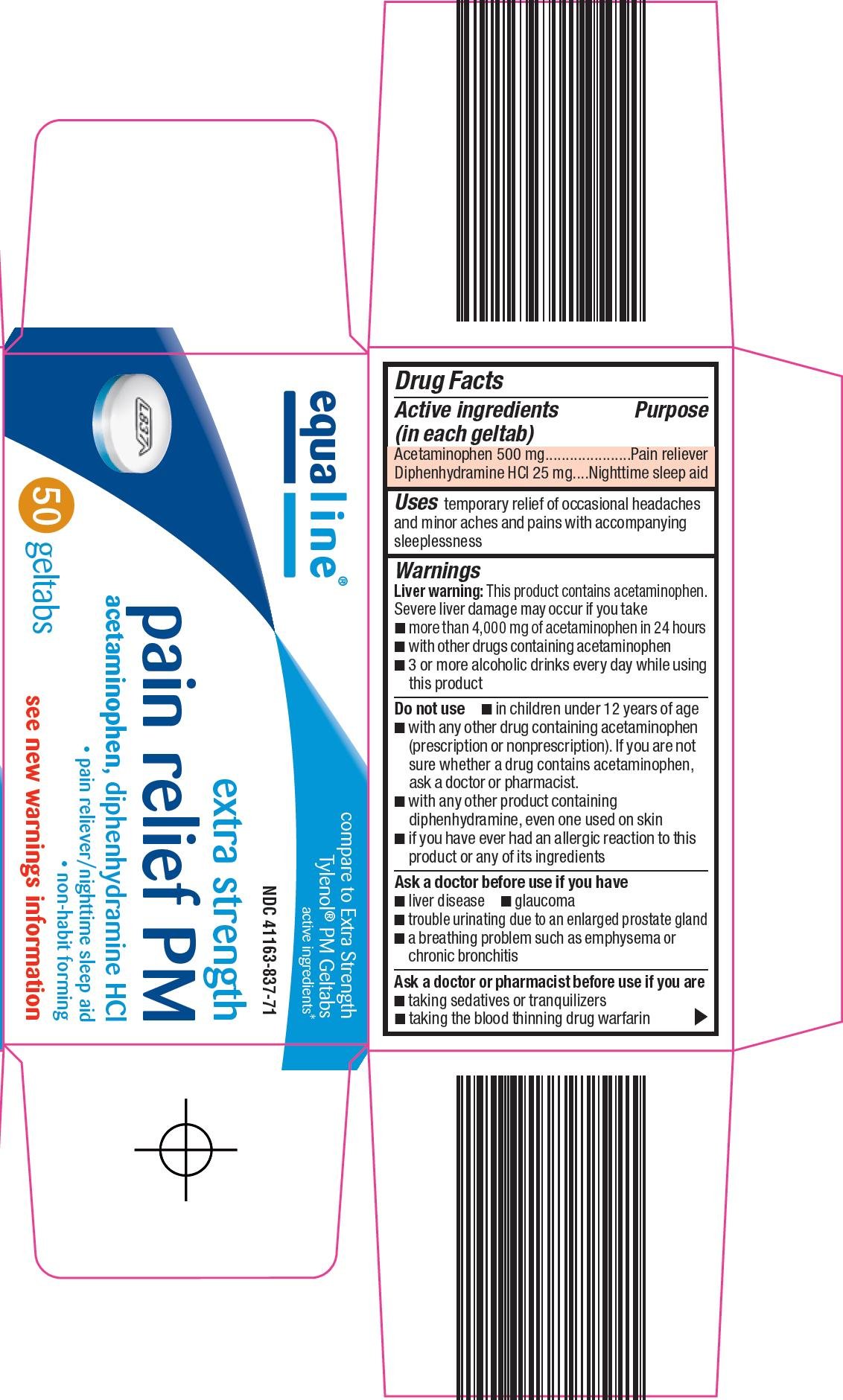 DRUG LABEL: equaline pain relief pm
NDC: 41163-837 | Form: TABLET, COATED
Manufacturer: Supervalu Inc
Category: otc | Type: HUMAN OTC DRUG LABEL
Date: 20101203

ACTIVE INGREDIENTS: ACETAMINOPHEN 500 mg/1 1; DIPHENHYDRAMINE HYDROCHLORIDE 25 mg/1 1
INACTIVE INGREDIENTS: CROSPOVIDONE; D&C RED NO. 33; EDETATE DISODIUM; FD&C BLUE NO. 1; GELATIN; GLYCERIN; HYPROMELLOSES; MAGNESIUM STEARATE; CELLULOSE, MICROCRYSTALLINE; POVIDONE; STEARIC ACID; TITANIUM DIOXIDE; POLYETHYLENE GLYCOLS

SuperValu Inc. Pain Relief PM Drug Facts

Active ingredient (in each geltab)

Acetaminophen 500 mg

Diphenhydramine HCl 25 mg

Purpose

Pain reliever

Nighttime sleep aid

Uses

temporary relief of occasional headaches and minor aches and pains with accompanying sleeplessness

Warnings

Liver warning: This product contains acetaminophen. Severe liver damage may occur if you take

- more than 4,000 mg of acetaminophen in 24 hours
- with other drugs containing acetaminophen
- 3 or more alcoholic drinks every day while using this product

Do not use

- in children under 12 years of age
- with any other drug containing acetaminophen (prescription or nonprescription). If you are not sure whether a drug contains acetaminophen, ask a doctor or pharmacist.
- with any other product containing diphenhydramine, even one used on skin
- if you have ever had an allergic reaction to this product or any of its ingredients

Ask a doctor before use if you have

- liver disease
- glaucoma
- trouble urinating due to an enlarged prostate gland
- a breathing problem such as emphysema or chronic bronchitis

Ask a doctor or pharmacist before use if you are

- taking sedatives or tranquilizers
- taking the blood thinning drug warfarin

When using this product

- drowsiness will occur
- avoid alcoholic drinks
- do not drive a motor vehicle or operate machinery

Stop use and ask a doctor if

- sleeplessness lasts continuously for more than 2 weeks. Insomnia may be a symptom of serious underlying medical illness.
- pain gets worse or lasts more than 10 days
- fever gets worse or lasts more than 3 days
- redness or swelling is present
- new symptoms occur

These could be signs of a serious condition.

If pregnant or breast-feeding,

ask a health professional before use.

Keep out of reach of children.

In case of overdose, get medical help or contact a Poison Control Center right away. (1-800-222-1222) Quick medical attention is critical for adults as well as for children even if you do not notice any signs or symptoms.

Directions

- do not take more than directed (see Liver warning).

Adults and children 12 years and over:

- take 2 geltabs at bedtime
- do not take more than 2 geltabs of this product in 24 hours

Children under 12 years: do not use this adult product in children under 12 years of age; this will provide more than the recommended dose (overdose) and may cause liver damage

Other information

- store at 20°-25°C (68°-77°F)

Inactive ingredients

crospovidone, D&C red no. 33, edetate disodium, edible ink, FD&C blue no. 1, gelatin, glycerin, hypromellose, magnesium stearate, microcrystalline cellulose, polyethylene glycol, povidone, pregelatinized starch, sodium starch glycolate, stearic acid, titanium dioxide

Questions or comments?

1-877-932-7948

Package/Label Principal Display Panel

compare to Extra Strength Tylenol® PM Geltabs active ingredients

extra strength

pain relief PM

acetaminophen, diphenhydramine HCl

pain reliever/nighttime sleep aid

non-habit forming

see new warnings information

Pain Relief PM Carton Image 1
Pain Relief PM Carton Image 2